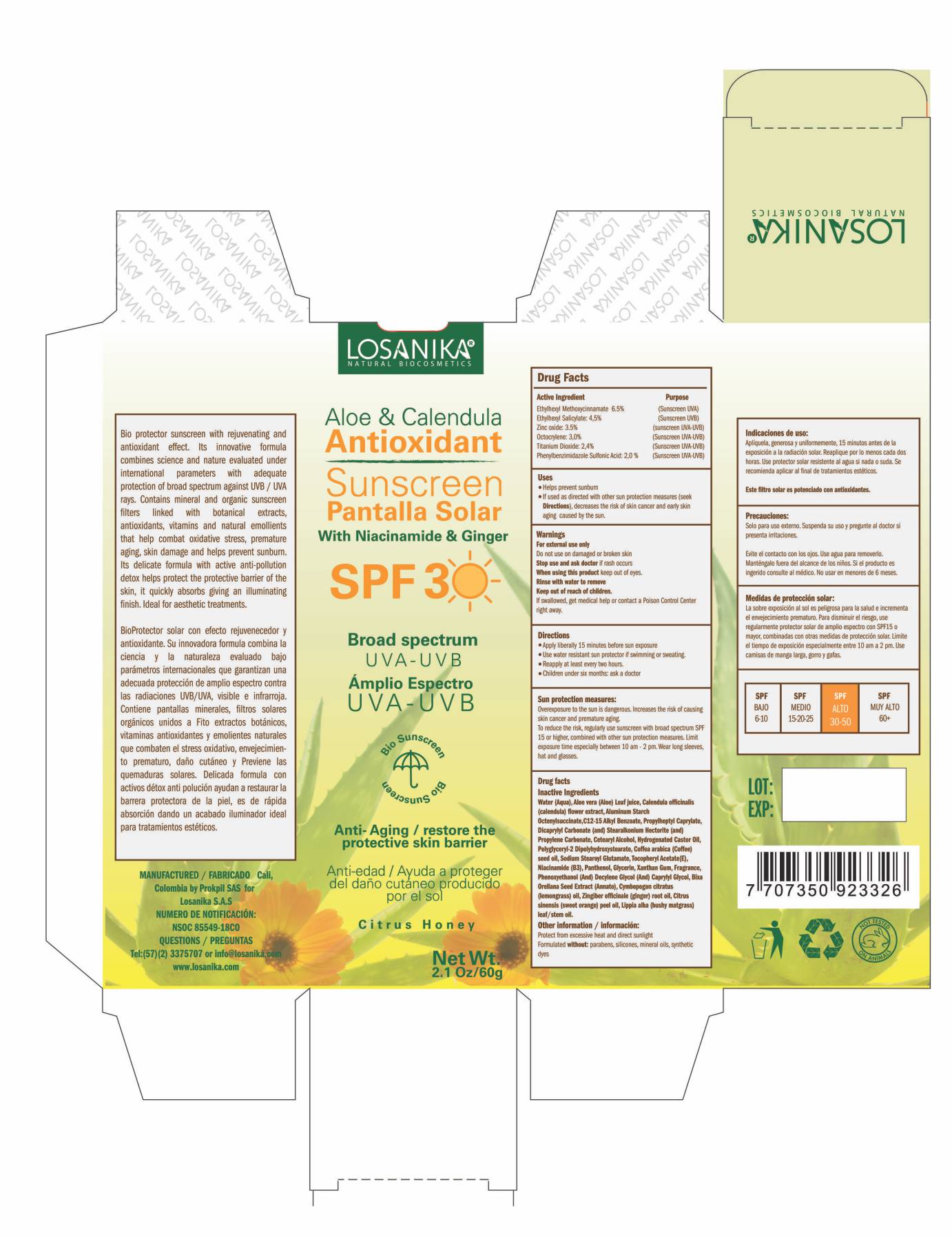 DRUG LABEL: OCTISALATE,OCTOCRYLENE,OCTINOXATE,ZINC OXIDE,TITANIUM DIOXIDE,ENSULIZOLE
NDC: 71801-542 | Form: CREAM
Manufacturer: PROKPIL SAS
Category: otc | Type: HUMAN OTC DRUG LABEL
Date: 20210302

ACTIVE INGREDIENTS: TITANIUM DIOXIDE 2.4 g/100 g; OCTOCRYLENE 3 g/100 g; ENSULIZOLE 2 g/100 g; OCTINOXATE 6.5 g/100 g; OCTISALATE 4.5 g/100 g; ZINC OXIDE 3.5 g/100 g
INACTIVE INGREDIENTS: ALKYL (C12-15) BENZOATE; PROPYLHEPTYL CAPRYLATE; HYDROGENATED CASTOR OIL; POLYGLYCERYL-2 DIPOLYHYDROXYSTEARATE; ALPHA-TOCOPHEROL ACETATE; BIXA ORELLANA SEED; NIACINAMIDE; WEST INDIAN LEMONGRASS OIL; PHENOXYETHANOL; DECYLENE GLYCOL; GINGER OIL; XANTHAN GUM; CETOSTEARYL ALCOHOL; SODIUM STEAROYL GLUTAMATE; WATER; DICAPRYLYL CARBONATE; STEARALKONIUM HECTORITE; ALUMINUM STARCH OCTENYLSUCCINATE; ARABICA COFFEE OIL; PANTHENOL; CAPRYLYL GLYCOL; LIPPIA ALBA WHOLE; ORANGE OIL; GLYCERIN; ALOE VERA LEAF; CALENDULA OFFICINALIS FLOWER; PROPYLENE CARBONATE

ALOE & CALENDUAL ANTIOXIDENT SUNSCREEN BROAD SPECTRUM SPF30

LOSANIKA ALOE & CALENDULA ANTIOXIDANT SUNSCREEN BROAD SPECTRUM SPF 30 - ENSULIZOLE 2.0 %, TITANIUM DIOXIDE 2.4 %, OCTOCRYLENE 3.0 %, ZINC OXIDE 3.5 %, OCTISALATE 4.5 %, OCTINOXATE 6.5 %

Disclaimer: Most OTC drugs are not reviewed and approved by FDA, however they maybe marketed if they comply with

regulations and policies. FDA has not evaluated weather this product complies.

PURPOSE:

SUNSCREEN

ACTIVE INGREDIENTS:

ENSULIZOLE 2.0 %

TITANIUM DIOXIDE 2.4 %

OCTOCRYLENE 3.0 %

ZINC OXIDE 3.5 %

OCTISALATE 4.5 %

OCTINOXATE 6.5 %

USES:

- Helps prevent sunburn
- If used as directed with other sun protection measures (seek Directions), decreases

the risk of skin cancer and early skin aging caused by the sun.

WARNING:

For external use only.

Do not use on damaged or broken skin.

WHEN USING THIS PRODUCT:

Keep out of eyes.

Rinse with water to remove.

STOP USE AND ASK A DOCTOR:

If rash or irritation develops or lasts.

KEEP OUT OF REACH OF CHILDREN:

If swallowed, get medical help or contact a Poison Control Center right away

DIRECTIONS:

Apply liberally 15 minutes before sun exposure

Use water resistant sun protector if swimming or sweating.
Reapply at least every two hours.
Children under six months: ask a doctor

Sun protection measures:

Overexposure to the sun is dangerous. Increases the risk of causing skin cancer and premature aging.

To reduce the risk, regularly use sunscreen with broad spectrum SPF 15 or higher, combined with other sun protection measures. Limit exposure time especially between 10 am - 2 pm. Wear long sleeves, hat and glasses.

INACTIVE INGREDIENTS:

Water (Aqua), Aloe vera (Aloe) Leaf juice, Calendula officinalis (calendula) flower extract, Aluminum Starch Octenylsuccinate,C12-15 Alkyl Benzoate, Propylheptyl Caprylate, Dicaprylyl Carbonate (and) Stearalkonium Hectorite (and) Propylene Carbonate, Cetearyl Alcohol, Hydrogenated Castor Oil, Polyglyceryl-2 Dipolyhydroxystearate, Coffea arabica (Coffee) seed oil, Sodium Stearoyl Glutamate, Tocopheryl Acetate(E), Niacinamide (B3), Panthenol, Glycerin, Xanthan Gum, Fragrance, Phenoxyethanol (And) Decylene Glycol (And) Caprylyl Glycol, Bixa Orellana Seed Extract (Annato), Cymbopogon citratus (lemongrass) oil, Zingiber officinale (ginger) root oil, Citrus sinensis (sweet orange) peel oil, Lippia alba (bushy matgrass) leaf/stem oil.

OTHER INFORMATION:

Protect from excessive heat and direct sunlight.

Formulated without: parabens, silicones, mineral oils, synthetic dyes.